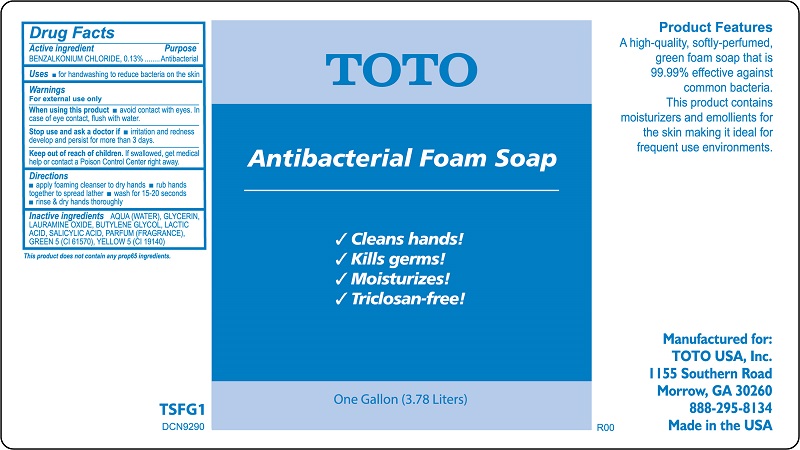 DRUG LABEL: Antibacterial Foam
NDC: 11084-021 | Form: SOLUTION
Manufacturer: SC Johnson Professional USA Inc.
Category: otc | Type: HUMAN OTC DRUG LABEL
Date: 20251223

ACTIVE INGREDIENTS: BENZALKONIUM CHLORIDE 1.3 g/1 L
INACTIVE INGREDIENTS: WATER; GLYCERIN; LAURAMINE OXIDE; BUTYLENE GLYCOL; LACTIC ACID, UNSPECIFIED FORM; SALICYLIC ACID; D&C GREEN NO. 5; FD&C YELLOW NO. 5

Drug Facts

Active ingredient

BENZALKONIUM CHLORIDE, 0.13%

Purpose

Antibacterial

Uses

for handwashing to reduce bacteria on the skin

Warnings

When using this product

avoid contact with eyes. In case of eye contact, flush with water.

Stop use and ask a doctor if

irritation and redness develop and persist for more than 3 days.

Keep out of reach of children.

If swallowed, get medical help or contact a Poison Control Center right away.

Directions

apply foaming cleanser to dry hands
rub hands together to spread lather
wash for 15-20 seconds
rinse & dry hands thoroughly

Inactive ingredients

AQUA (WATER), GLYCERIN, LAURAMINE OXIDE, BUTYLENE GLYCOL, LACTIC ACID, SALICYLIC ACID, PARFUM (FRAGRANCE), GREEN 5 (CI 61570), YELLOW 5 (CI 19140).

PACKAGE LABEL

This product does not contain any prop65 ingredients.

TSFG1

DCN9290

TOTO

Antibacterial Foam Soap

Cleans hands!

Kills germs!

Moisturizes!

Triclosan-free!

One Gallon (3.78 Liters)

Product Features

A high-quality , softly-perfumed, green foam soap that is 99.99% effective against common bacteria.

This product contains moisturizers and emollients for the skin making it ideal for frequent use environments.

Manufactured for:

TOTO USA, Inc.

1155 Southern Road

Morrow, GA 30260

888-295-8134

Made in the USA

R00